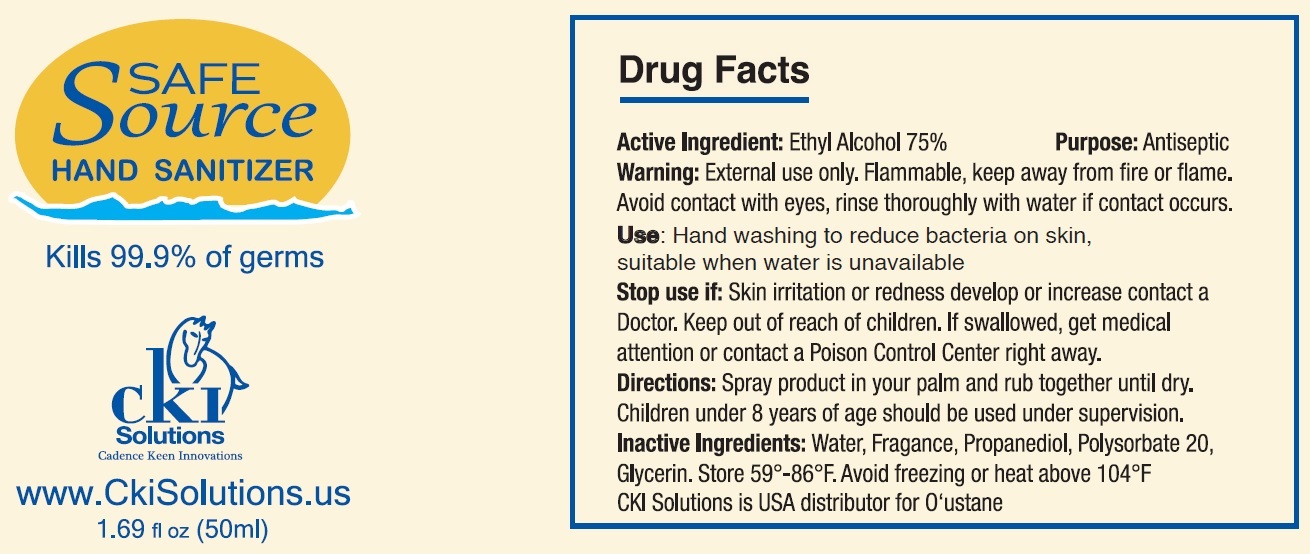 DRUG LABEL: Safe Source Hand Sanitizer
NDC: 79128-001 | Form: GEL
Manufacturer: Cadence Keen Innovations, Inc.
Category: otc | Type: HUMAN OTC DRUG LABEL
Date: 20200629

ACTIVE INGREDIENTS: ALCOHOL 0.75 mL/1 mL
INACTIVE INGREDIENTS: WATER; PROPANEDIOL; POLYSORBATE 20; GLYCERIN

Safe Source Hand Sanitizer

Active Ingredient:

Ethyl Alcohol 75%

Purpose

Antiseptic

Uses

Hand washing to reduce bacteria on skin, suitable when water is unavailable

Warnings

External Use only. Flammable, keep away from fire or flame.

Avoid contact with eyes, rinse thoroughly with water if contact occurs

Stop use if:

Skin irritation or redness develop or increase contact a doctor.

Keep out of reach of children.

If swallowed, get medical attention or contact a Poison Control Center right away.

Directions

- Spray product in your palm and rub together until dry.
- Children under 8 years of age should be used under supervision.

Inactive Ingredients

Water, Fragance, Propanediol, Polysorbate 20, Glycerin

Store 59°-86°F. Avoid freezing heat above 104°F

CKI Solutions is USA distributor for O'ustane